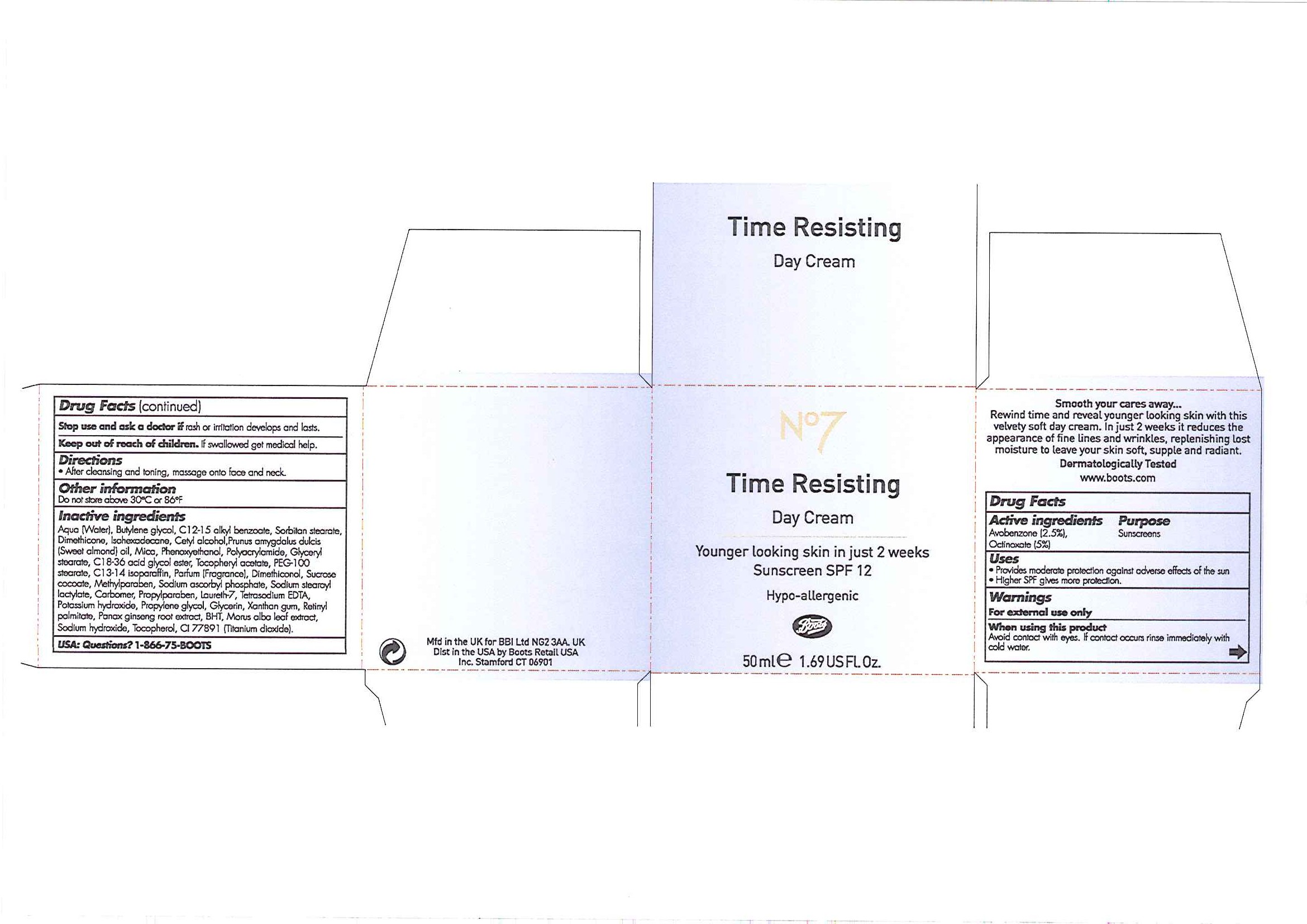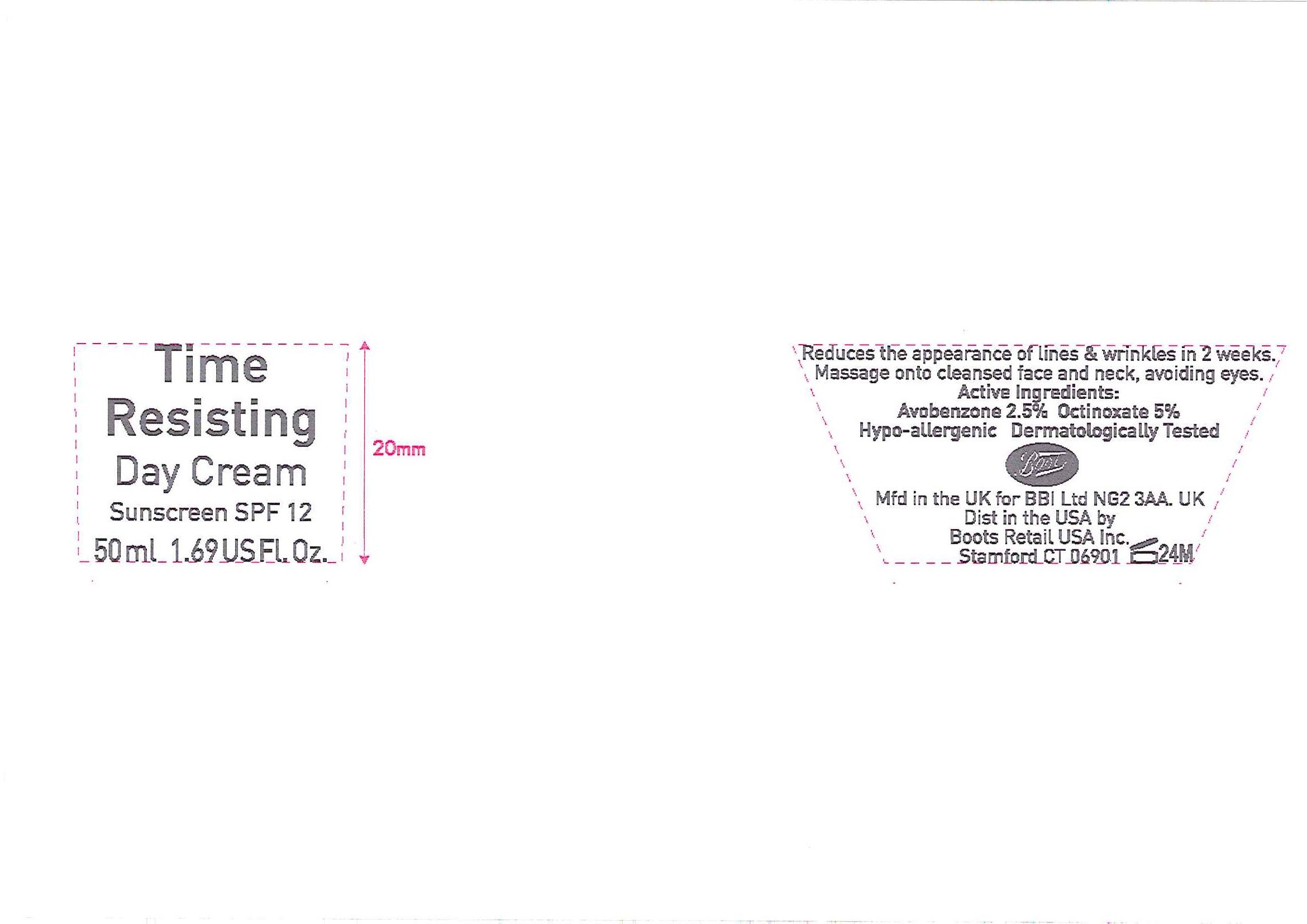 DRUG LABEL: No7 Time Resisting Day Sunscreen SPF 12
NDC: 11489-062 | Form: CREAM
Manufacturer: BCM Ltd
Category: otc | Type: HUMAN OTC DRUG LABEL
Date: 20101206

ACTIVE INGREDIENTS: OCTINOXATE 2.5 mL/50 mL; AVOBENZONE 1.25 mL/50 mL
INACTIVE INGREDIENTS: WATER; BUTYLENE GLYCOL; SORBITAN MONOSTEARATE; DIMETHICONE; CETYL ALCOHOL; ALMOND OIL; PHENOXYETHANOL; GLYCERYL MONOSTEARATE; .ALPHA.-TOCOPHEROL ACETATE, DL-; POLYOXYL 100 STEARATE; METHYLPARABEN; SODIUM ASCORBYL PHOSPHATE; CARBOMER HOMOPOLYMER TYPE C; PROPYLPARABEN; POTASSIUM HYDROXIDE; PROPYLENE GLYCOL; GLYCERIN; XANTHAN GUM; VITAMIN A PALMITATE; ASIAN GINSENG; BUTYLATED HYDROXYTOLUENE; SODIUM HYDROXIDE; ALPHA-TOCOPHEROL; TITANIUM DIOXIDE

Carton and jar labels

DESCRIPTION

No7 Time Resisting Day Cream Sunscreen SPF 12
Smooth your cares away ...
Rewind time and reveal younger looking skin with this velvety soft day cream. In just 2 weeks it reduces the appearance of fine lines and wrinkles, replenishing lost moisture to leave your skin soft, supple and radiant.
Dermatologically Tested
www.boots.com

Active ingredients Purpose
Avobenzone (2.5%)
Octinoxate (5%)

Uses

- Provides moderate protection against adverse effects of the sun
- Higher SPF gives more protection

Warnings

For external use only

When using this product

Avoid contact with eyes. If contact occurs rinse immediately with cold water.

Stop use and ask a doctor if rash or irritation develops and lasts.

Keep out of reach of children. If swallowed get medical help.

Directions

- After cleansing and toning, massage onto face and neck.

Other information
Do not store above 30oCor 86oF

Inactive ingredients

Aqua (Water), Butylene glycol, C12-15 alkyl benzoate, Sorbitan stearate, Dimethicone, Isohexadecane, Cetyl alcohol, Prunus amygdalus dulcis (Sweet almond oil), Mica, Phenoxyethanol, Polyacrylamide, Glyceryl stearate, C18-36 acid glycol ester, Tocopheryl acetate, PEG-100 stearate, C13-14 isoparaffin, Parfum (Fragrance), Dimethiconol, Sucrose cocoate, Methylparaben, Sodium ascorbyl phosphate, Sodium stearoyl lactylate, Carbomer, Propylparaben, Laureth-7, Tetrasodium EDTA, Potassium hydroxide, Propylene glycol, Glycerin, Xanthan gum, Retinyl palmitate, Panax ginseng root extract, BHT, Morus alba leaf extract, Sodium hydroxide, Tocopherol, CI 77891 (Titanium dixoide).

USA: Questions? 1-866-75-BOOTS

PATIENT COUNSELING INFORMATION

Mfd in the UK for BBI Ltd NG2 3AA. UK
Dist in the USA by Boots Retail USA Inc. Stamford CT 06901

DESCRIPTION

Jar label
Reduces the appearance of lines and wrinkles in 2 weeks.
Massage onto cleansed face and neck, avoiding eyes.
Hypo-allergenic.
Dermatologically Tested

Active ingredients:
Avobenzone 2.5%
Octinoxate 5%

PATIENT COUNSELING INFORMATION

Boots

Mfd in the UK for BBI Ltd NG2 3AA. UK

Dist in the USA by Boots Retail USA Inc. Stamford CT 06901

PACKAGE LABEL

No7

Time Resisting

Day Cream

Younger looking skin in just 2 weeks

Sunscreen SPF 12

Hypo-allergenic

Boots

50ml e 1.69 US Fl. Oz

Time Resisting Day Cream carton.jpg

PACKAGE LABEL

Time Resisting

Day Cream

Sunscreen SPF 12

50ml 1.69 US Fl. Oz

Time Resisting Day Cream jar.jpg